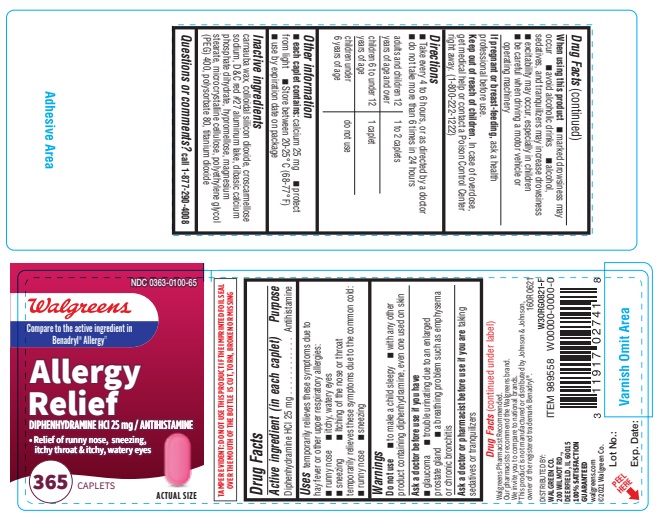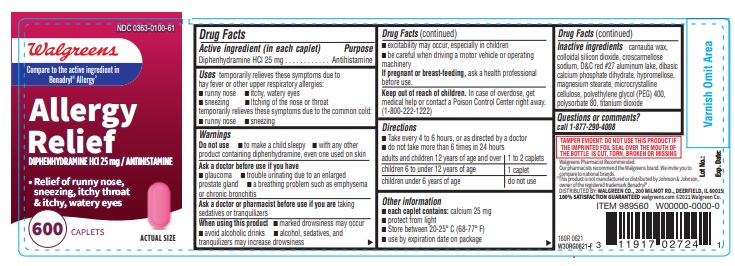 DRUG LABEL: ALLERGY RELIEF
NDC: 0363-0100 | Form: TABLET, FILM COATED
Manufacturer: WALGREENS
Category: otc | Type: HUMAN OTC DRUG LABEL
Date: 20250625

ACTIVE INGREDIENTS: DIPHENHYDRAMINE HYDROCHLORIDE 25 mg/1 1
INACTIVE INGREDIENTS: DIBASIC CALCIUM PHOSPHATE DIHYDRATE; CARNAUBA WAX; SILICON DIOXIDE; MAGNESIUM STEARATE; POLYSORBATE 80; CROSCARMELLOSE SODIUM; D&C RED NO. 27 ALUMINUM LAKE; CELLULOSE, MICROCRYSTALLINE; HYPROMELLOSES; POLYETHYLENE GLYCOL 400; TITANIUM DIOXIDE

160R Walgreens 0363 0100 Diphenhydramine Hydrochloride 25 mg tablets

Active ingredient (in each caplet)

Diphenhydramine HCl 25 mg

Purpose

Antihistamine

Uses

temporarily relieves these symptoms due to hay fever or other upper respiratory allergies:

- runny nose
- itchy, watery eyes
- sneezing
- Itching of the nose or throat

temporarily relieves these symptoms due to the common cold:

- runny nose
- sneezing

Warnings

Ask a doctor before use if you have

- glaucoma
- trouble urinating due to enlarged prostrate gland
- a breathing problem such as emphysema or chronic bronchitis

Do not use

- to make a child sleepy
- with any other product containing diphenhydramine, even one used on skin

Ask a doctor or pharmacist before use if you are taking sedatives or tranquilizers

When using this product

- marked drowsiness may occur
- avoid alcoholic drinks
- alcohol, sedatives, and tranquilizers may increase drowsiness
- excitability may occur, especially in children
- be careful when driving a motor vehicle or operating machinery

PREGNANCY OR BREAST FEEDING

If pregnant or breast-feeding, ask a health professional before use.

Keep out of reach of children. In case of overdose, get medical help or contact a Poison Control Center right away. (1-800-222-1222)

Directions

- Take every 4 to 6 hours, or as directed by a doctor
- do not take more than 6 times in 24 hours

adults and children 12 years of age and over: 1 to 2 caplets

children 6 to under 12 years of age: 1 caplet

children under 6 years of age: do not use

Other information

- each caplet contains: calcium 25 mg
- protect from light
- Store between 20-25°C (68-77° F)
- use by expiration date on package

INACTIVE INGREDIENT

Inactive ingredients carnauba wax, colloidal silicon dioxide, croscarmellose sodium, D&C red #27 aluminum lake, dibasic calcium phosphate dihydrate, hypromellose, magnesium stearate, microcrystalline cellulose, polyethylene glycol (PEG) 400, polysorbate 80, titanium dioxide